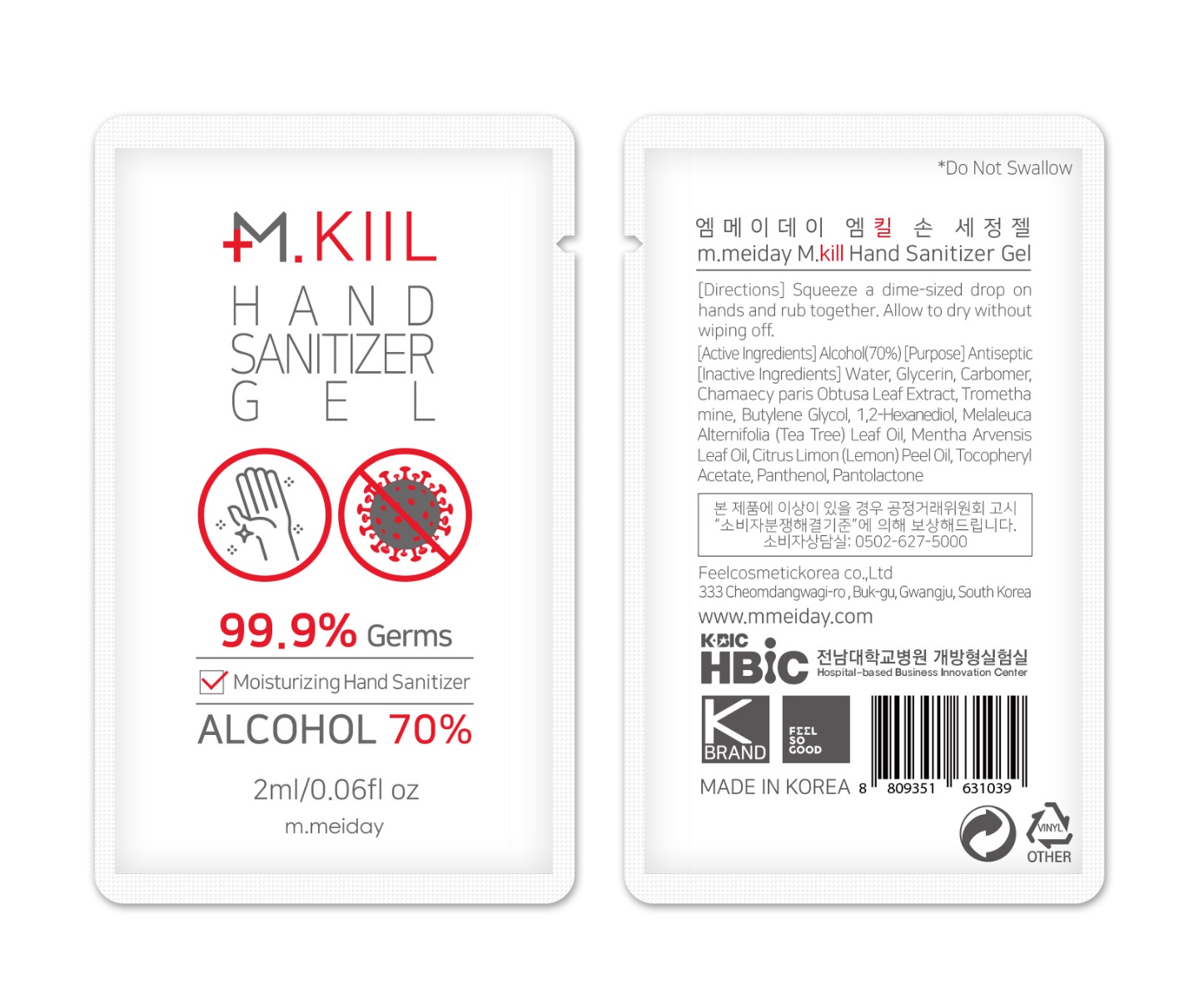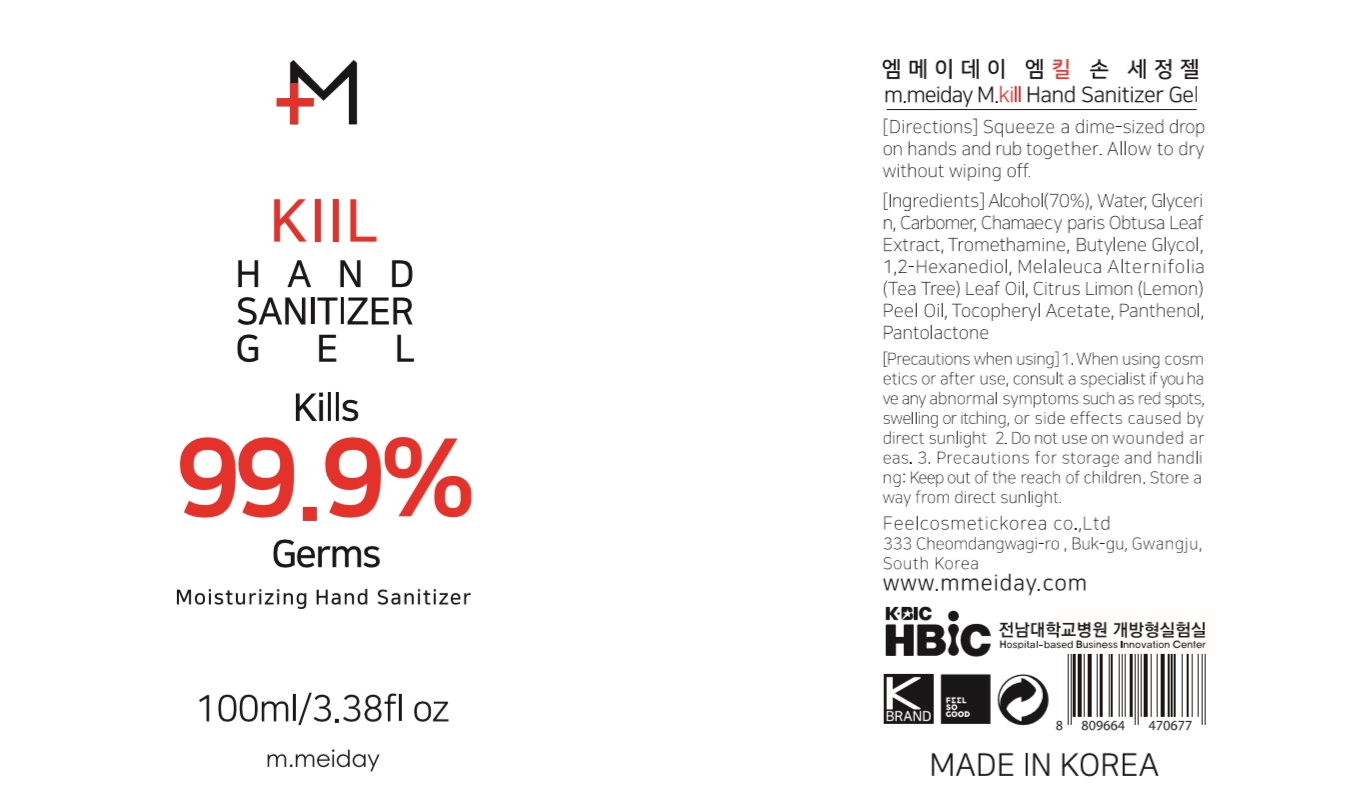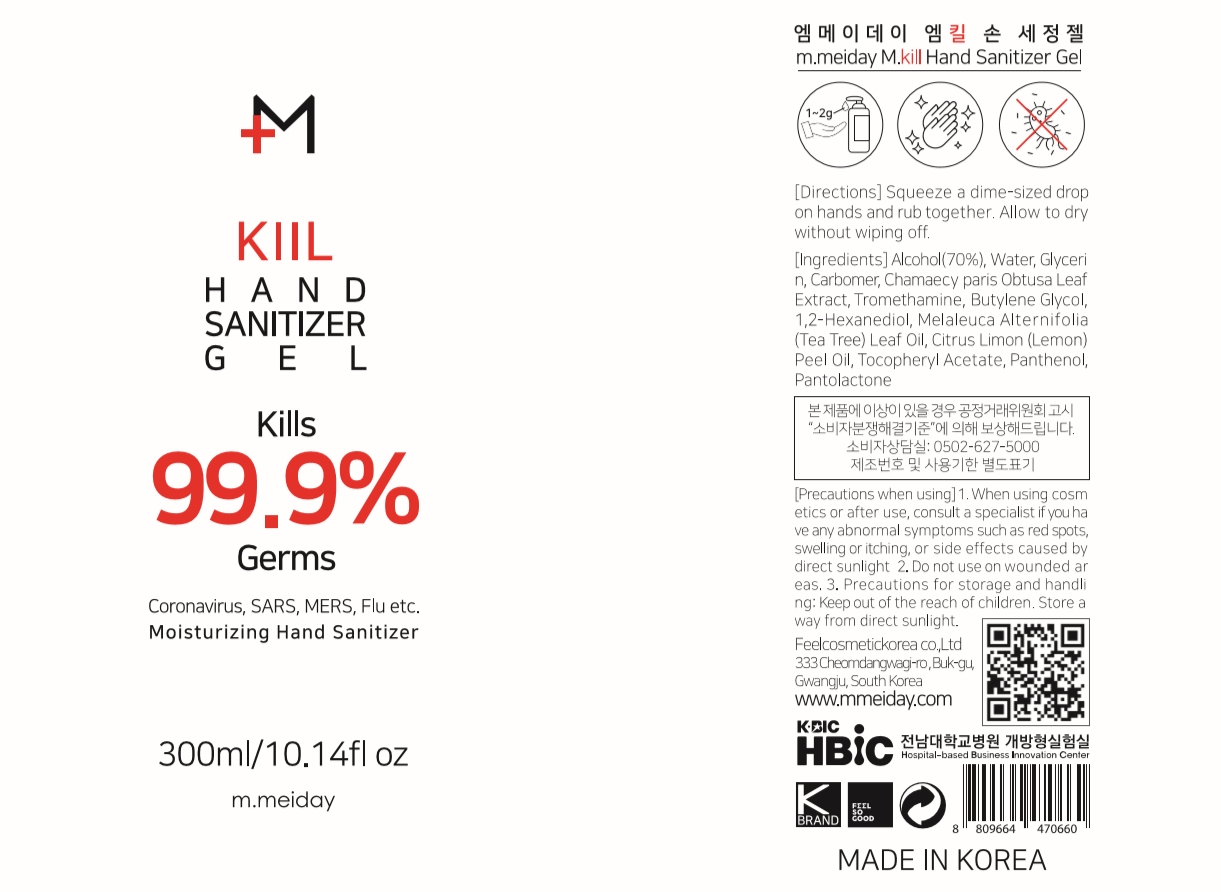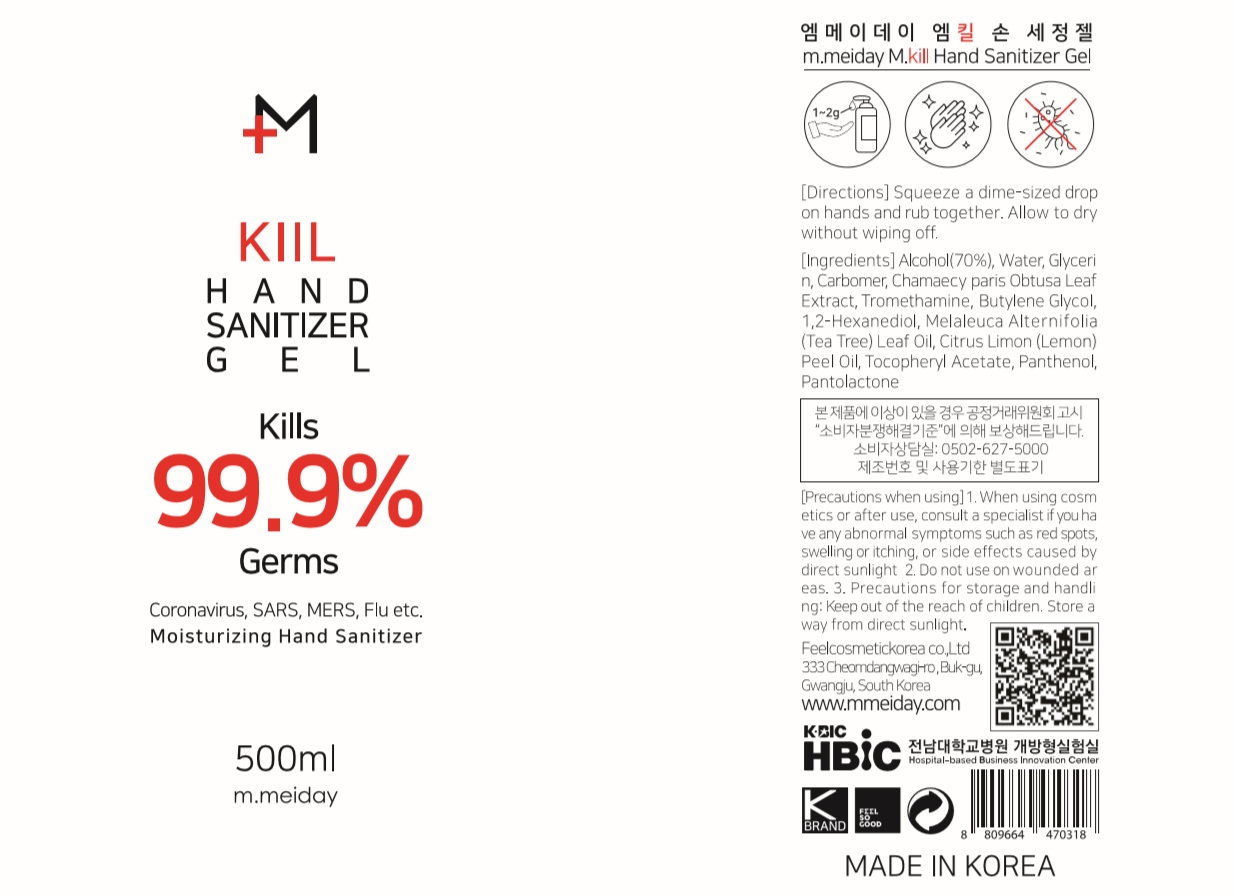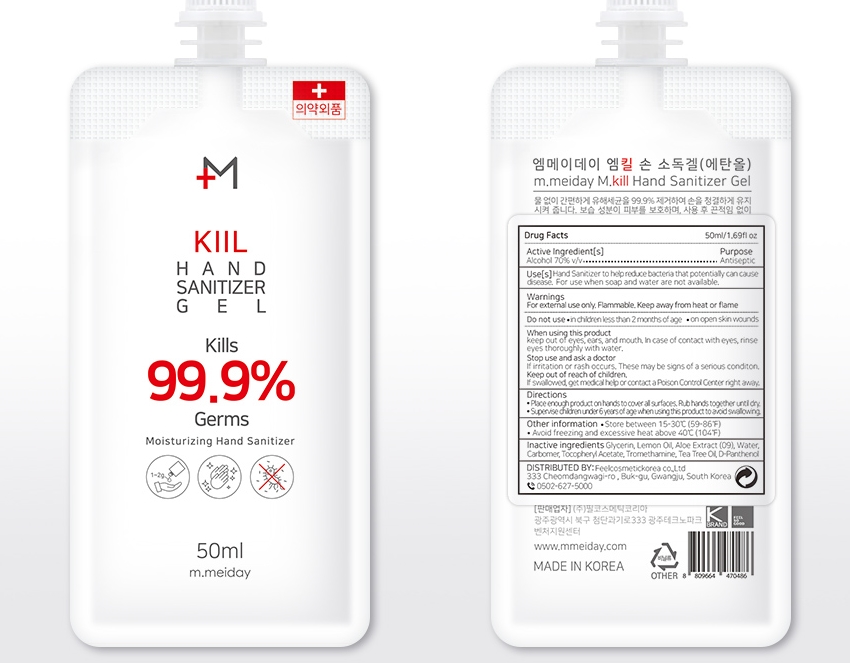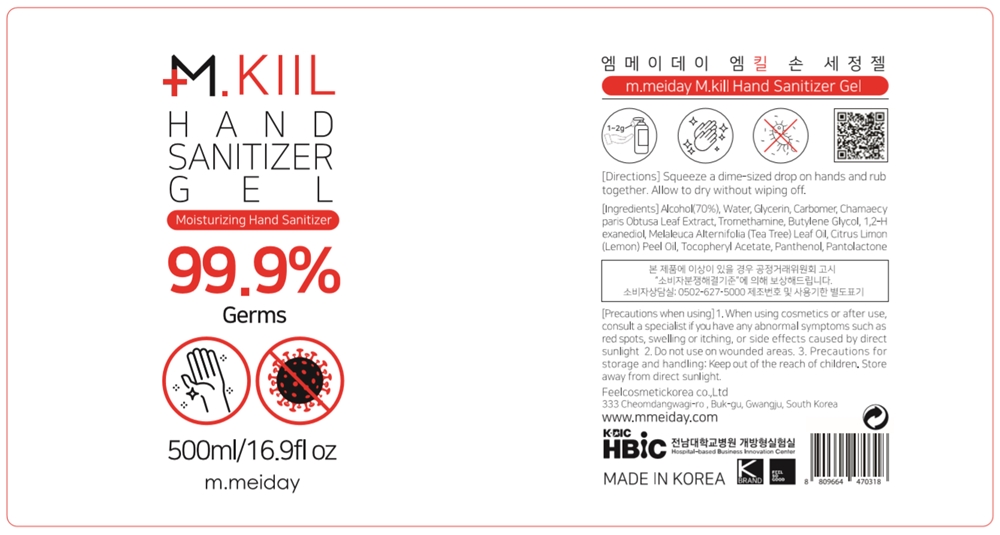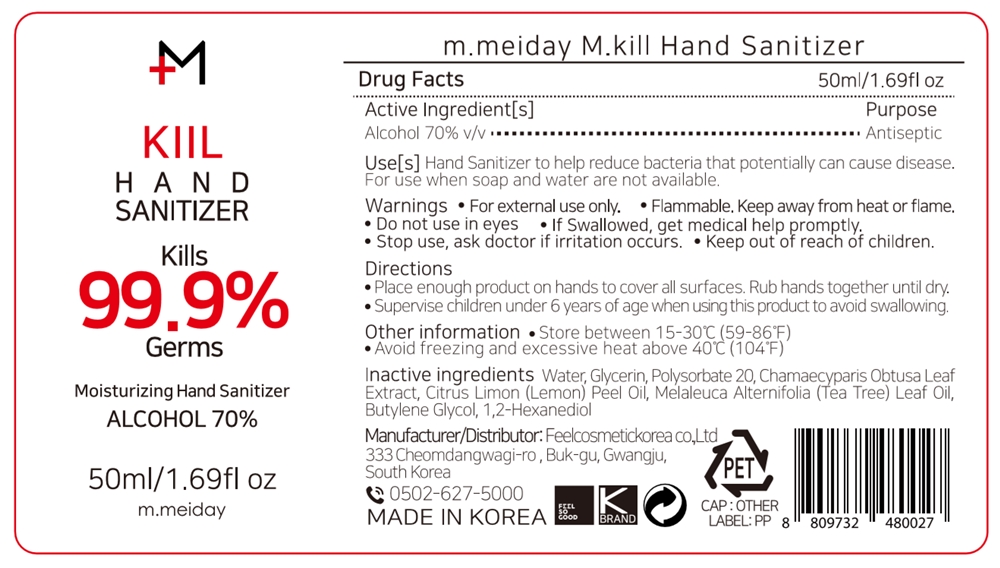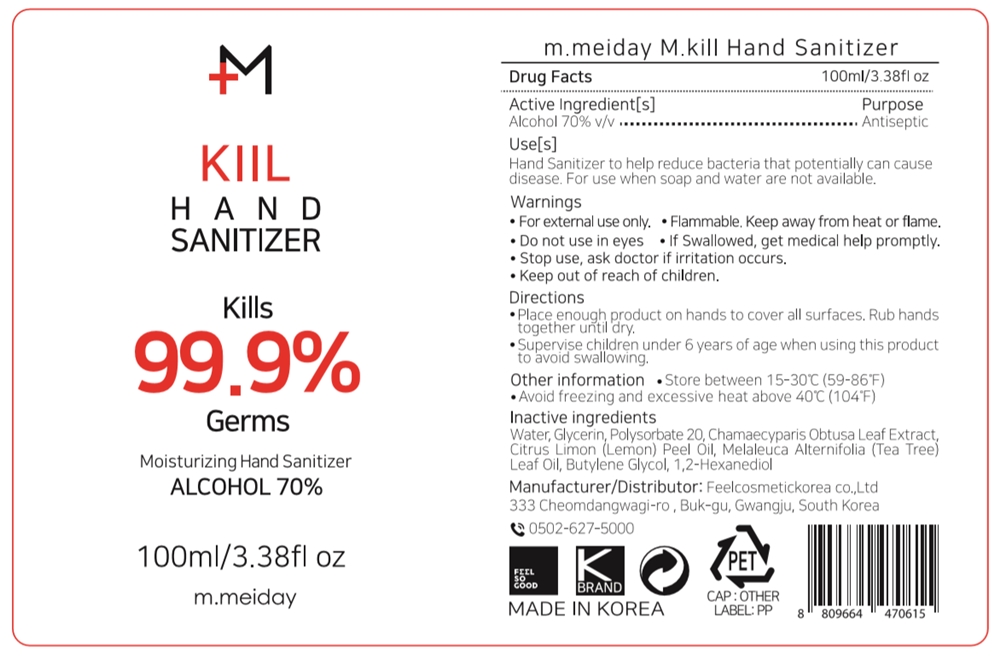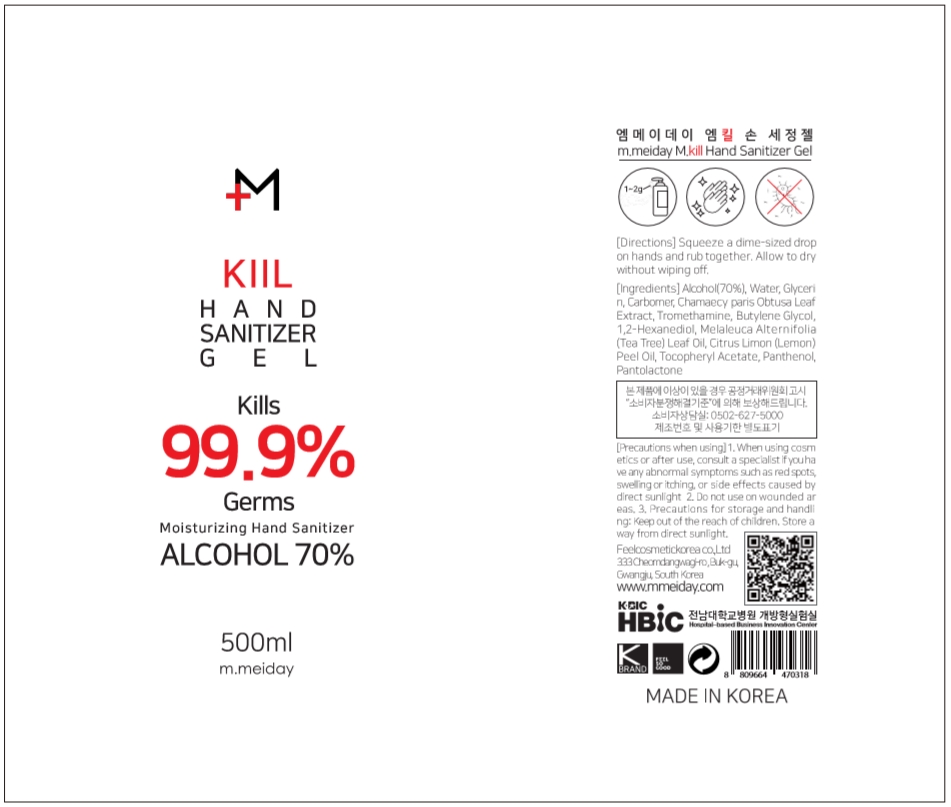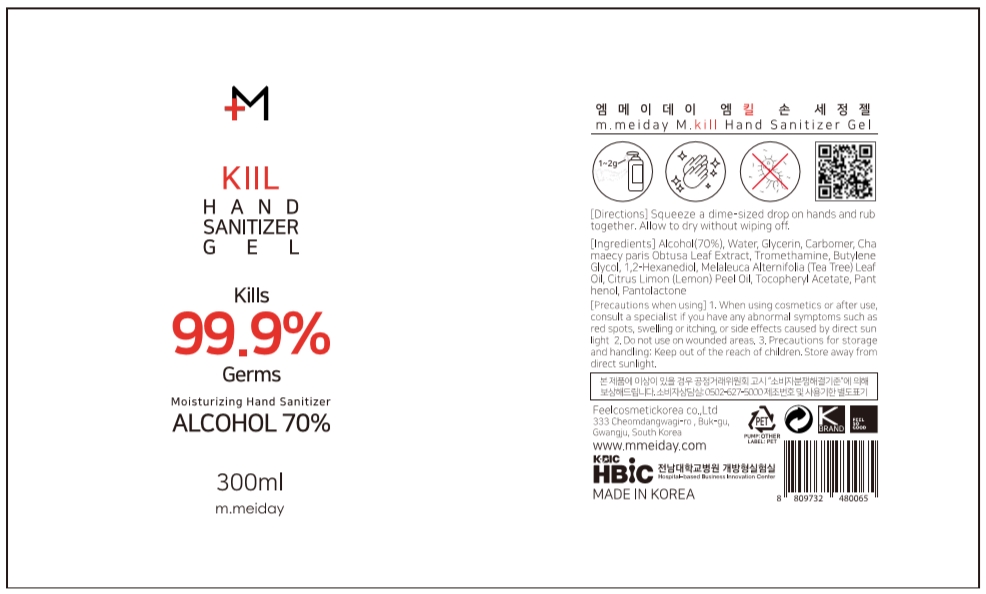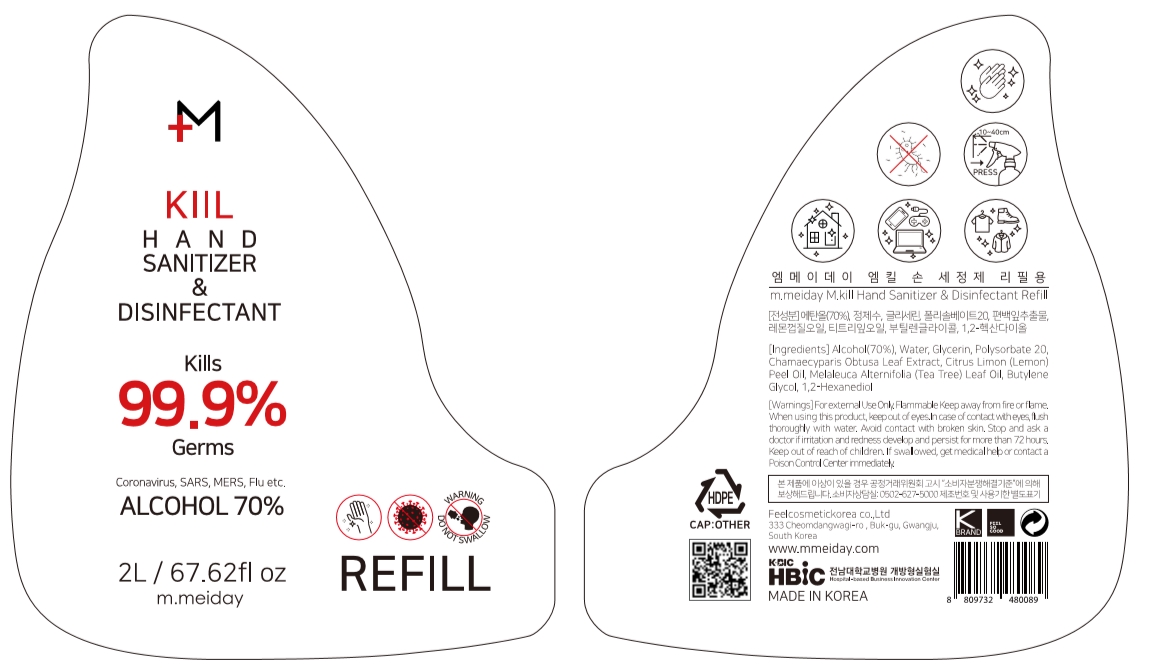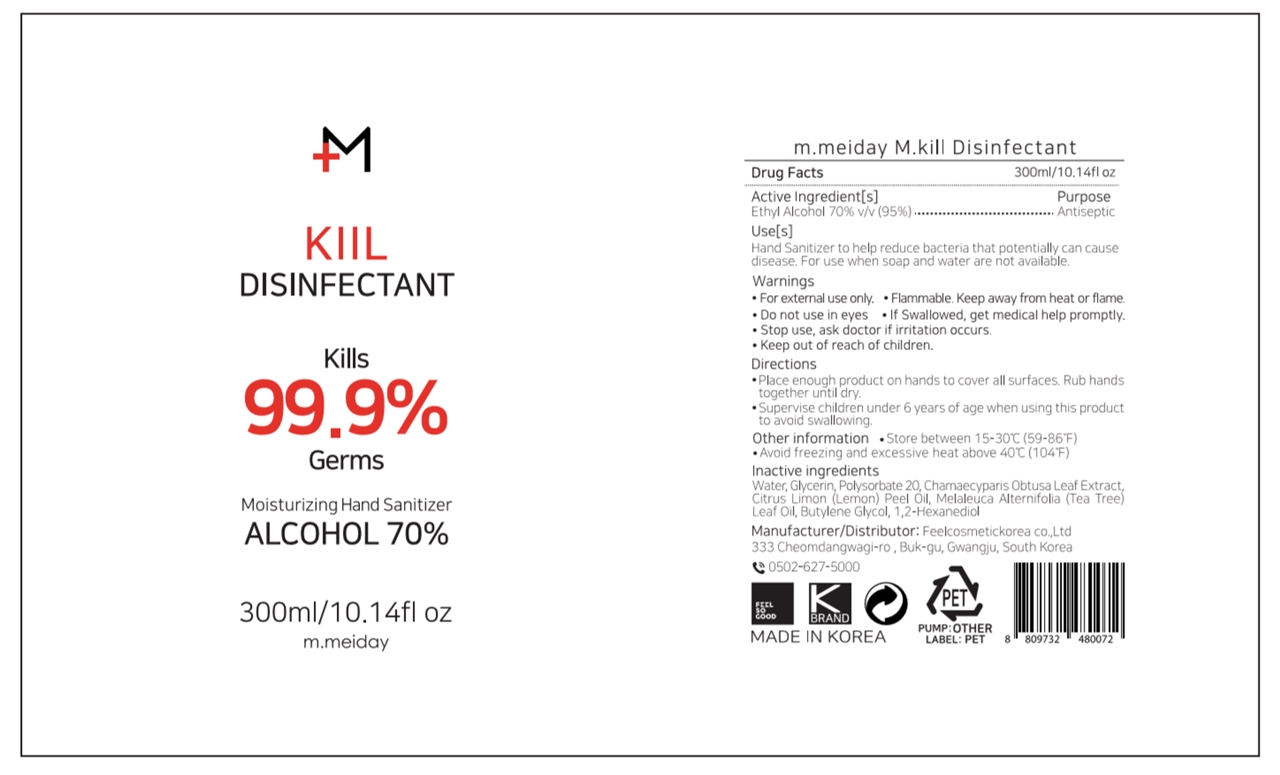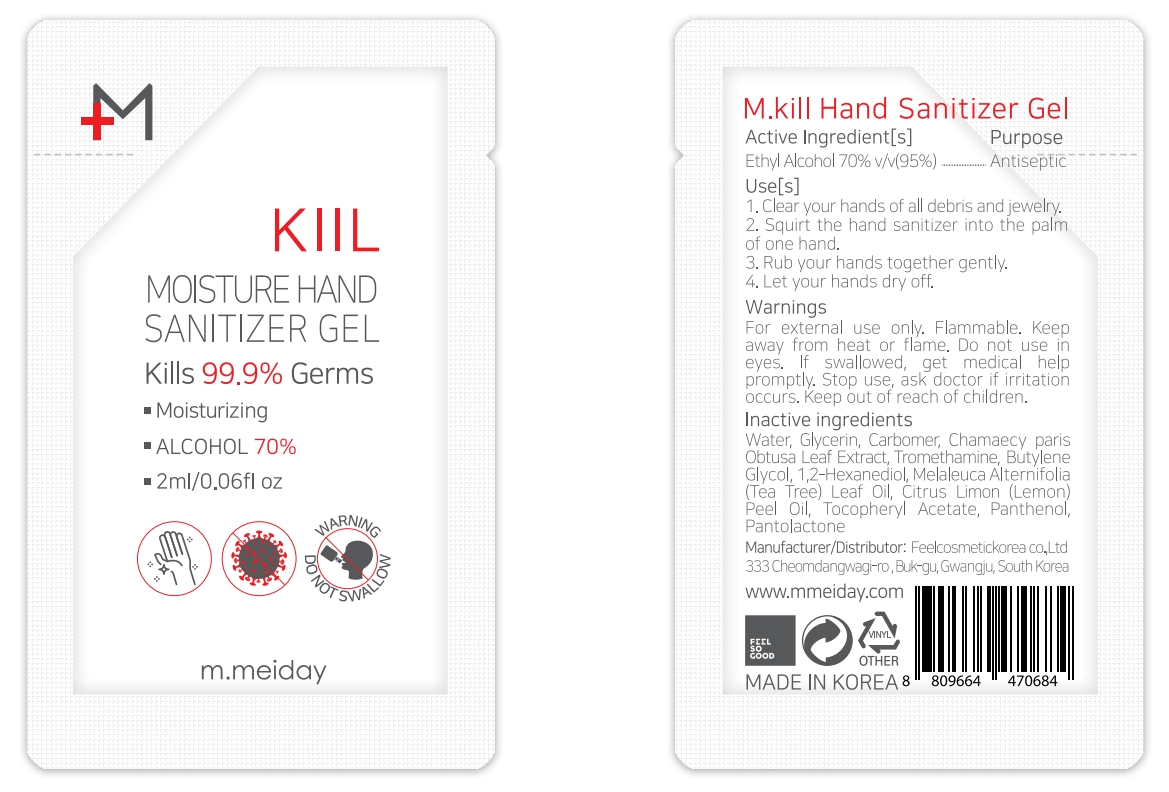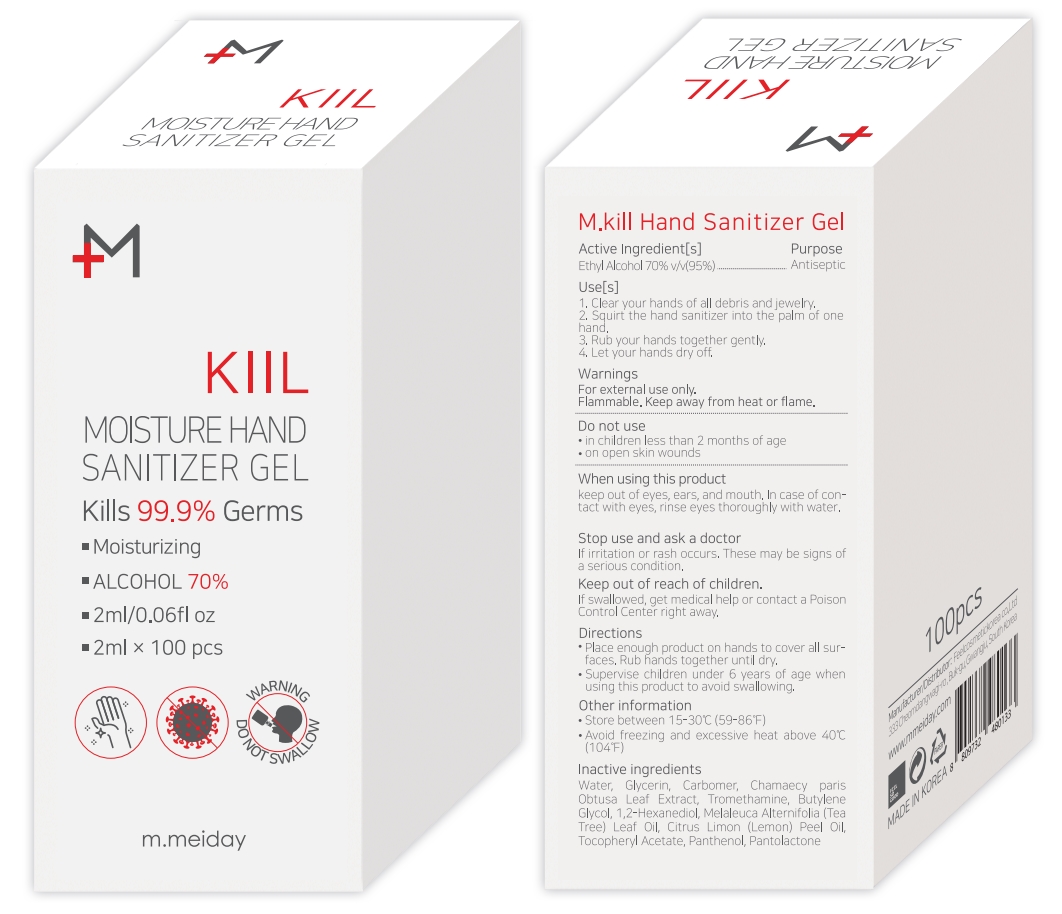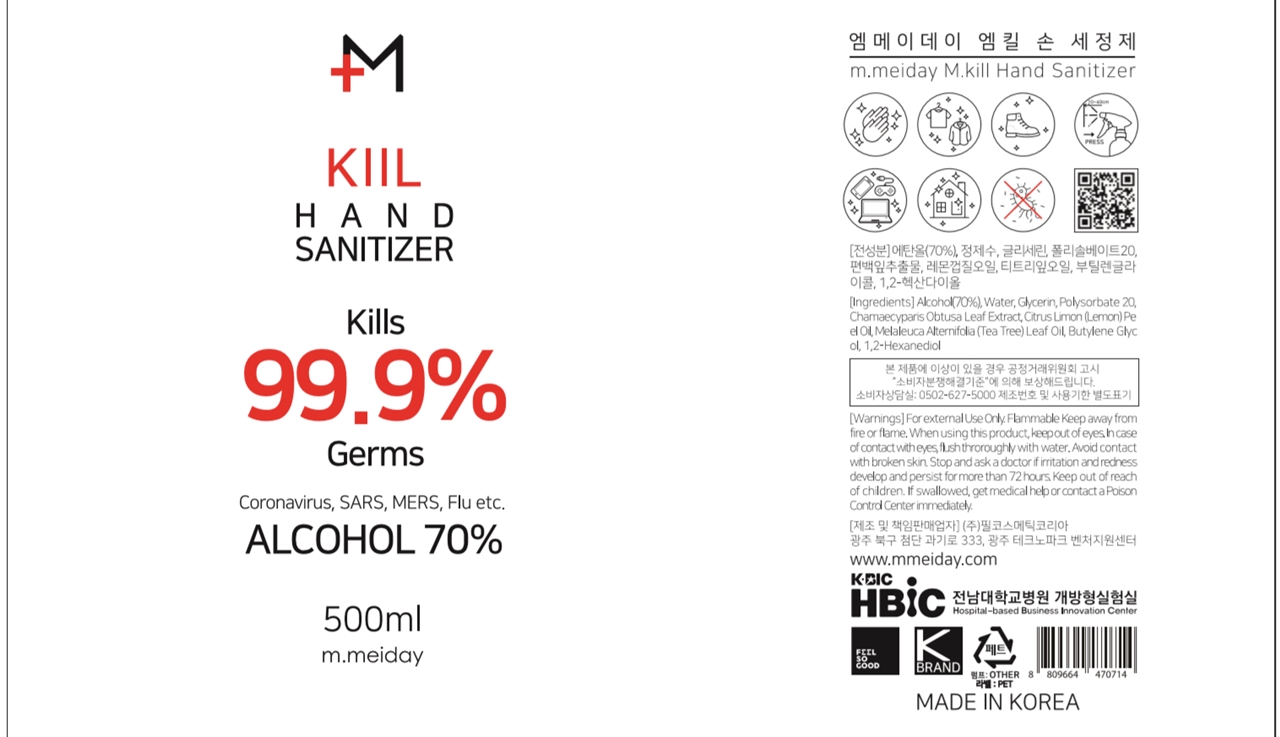 DRUG LABEL: m.meiday M.kill Hand Sanitizer Gel
NDC: 74454-319 | Form: GEL
Manufacturer: FEEL COSMETIC KOREA CO., LTD
Category: otc | Type: HUMAN OTC DRUG LABEL
Date: 20200805

ACTIVE INGREDIENTS: ALCOHOL 70 mL/100 mL
INACTIVE INGREDIENTS: ALPHA-TOCOPHEROL ACETATE 0.1 mL/100 mL; PANTOLACTONE, (R)- 0.001 mL/100 mL; BUTYLENE GLYCOL 0.2 mL/100 mL; LEMON OIL 0.1 mL/100 mL; TEA TREE OIL 0.1 mL/100 mL; WATER 25.349 mL/100 mL; CARBOMER HOMOPOLYMER, UNSPECIFIED TYPE 0.5 mL/100 mL; GLYCERIN 3 mL/100 mL; TROMETHAMINE 0.1 mL/100 mL; PANTHENOL 0.05 mL/100 mL; CHAMAECYPARIS OBTUSA LEAF 0.3 mL/100 mL; 1,2-HEXANEDIOL 0.2 mL/100 mL

74454-319

Active Ingredient

Alcohol 70%

Purpose

Antiseptic

Inactive Ingredient

Water, Glycerin, Carbomer, Chamaecy paris Obtusa Leaf Extract, Tromethamine, Butylene Glycol, 1,2-Hexanediol, Melaleuca Alternifolia (Tea Tree) Leaf Oil, Citrus Limon (Lemon) Peel Oil, Tocopheryl Acetate, Panthenol, Pantolactone

Directions

Squeeze a dime-sized drop on hands and rub together. Allow to dry without wiping off.

Warnings

For external use only. Flammable. Keep away from heat or flame.

Do not use

in children less than 2 months of age

on open skin wounds

When using this product

keep out of eyes, ears, and mouth. In case of contact with eyes, rinse eyes thoroughly with water.

Stop use and ask a doctor

if irritation or rash occurs. These may be signs of a serious condition.

Keep out of reach of children.

If swallowed, get medical help or contact a Poison Control Center right away.

Use

Hand Sanitizer to help reduce bacteria that potentially can cause disease. For use when soap and water are not available.

Other information

Store between 15-30C (59-86F)

Avoid freezing and excessive heat above 40C (104F)